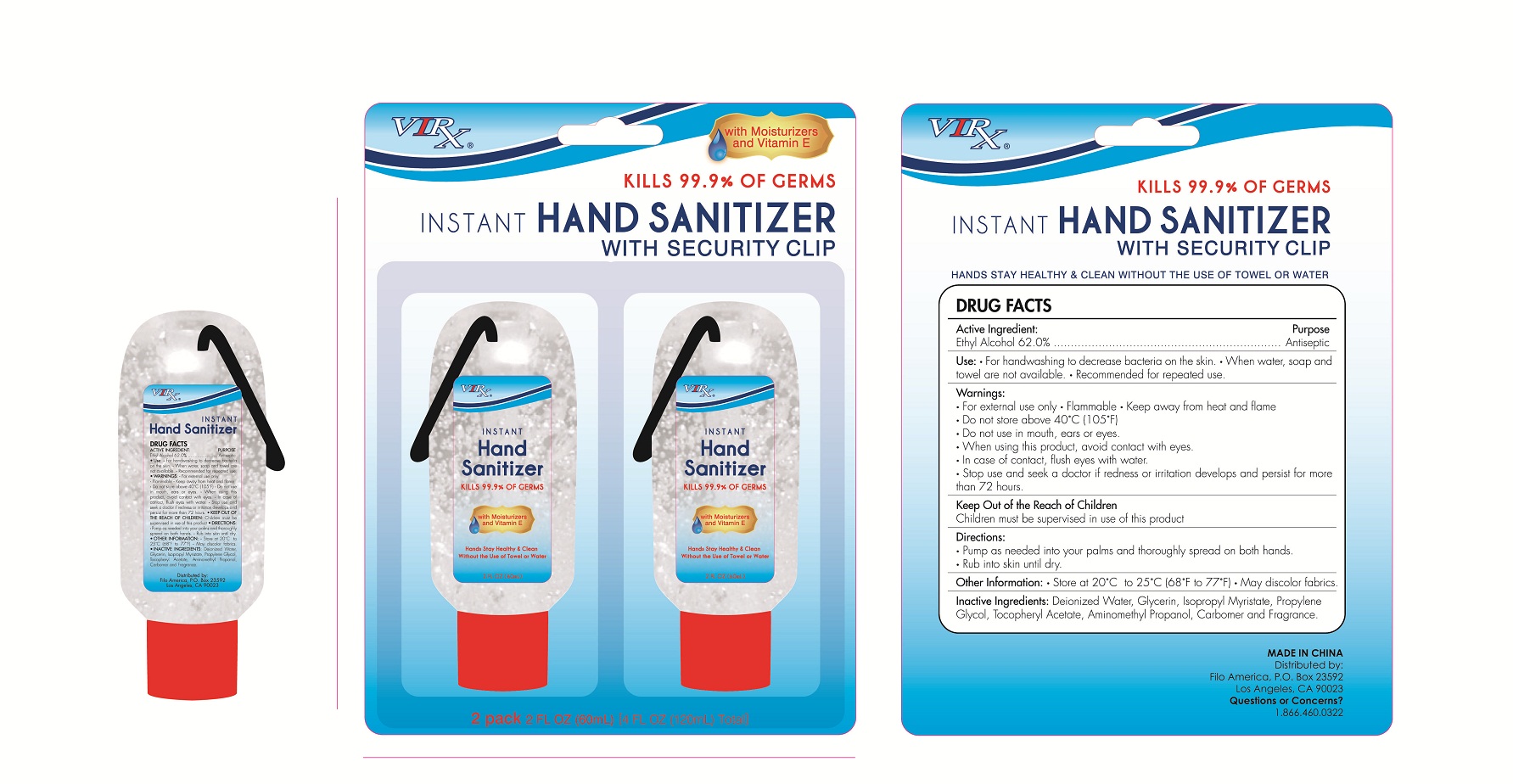 DRUG LABEL: Virx Instant Hand Sanitizer with security clip
NDC: 50438-200 | Form: GEL
Manufacturer: Filo America
Category: otc | Type: HUMAN OTC DRUG LABEL
Date: 20130730

ACTIVE INGREDIENTS: alcohol 62 mL/100 mL
INACTIVE INGREDIENTS: WATER; PROPYLENE GLYCOL; ALOE VERA LEAF; CARBOMER 934; GLYCERIN; .ALPHA.-TOCOPHEROL ACETATE, D-; TROLAMINE

Drug facts

Active ingredient Purpose

Alcohol 62% ... Antiseptic

PURPOSE

For hand washing to decrease bacteria on the skin. When water, soap and towel are not available; Recommended for repeated use.

KEEP OUT OF REACH OF CHILDREN

Children must be supervised in use of this product.

INDICATIONS AND USAGE

keep out of eyes

when water, soap and towel are not available

WARNINGS

For external use only.
Flammable. Keep away from hear or flame.

Don't store above 40•C (105•F)

When using this products, avoid contact with eyes. In case of contact, flush eyes with water and seek medical advise.

Stop using and seek a doctor, if irritation or redness persist for more than 72 hours.

DOSAGE AND ADMINISTRATION

Pump as needed into your palms and thoroughly spread on both hands. Rub into skin until dry.

INACTIVE INGREDIENT

Water, Carbomer, Glycerin, Propylene Glycol, Triethanolamine, Aloe Barbadensis Leaf Juice, Tocopheryl Acetate, Fragrance